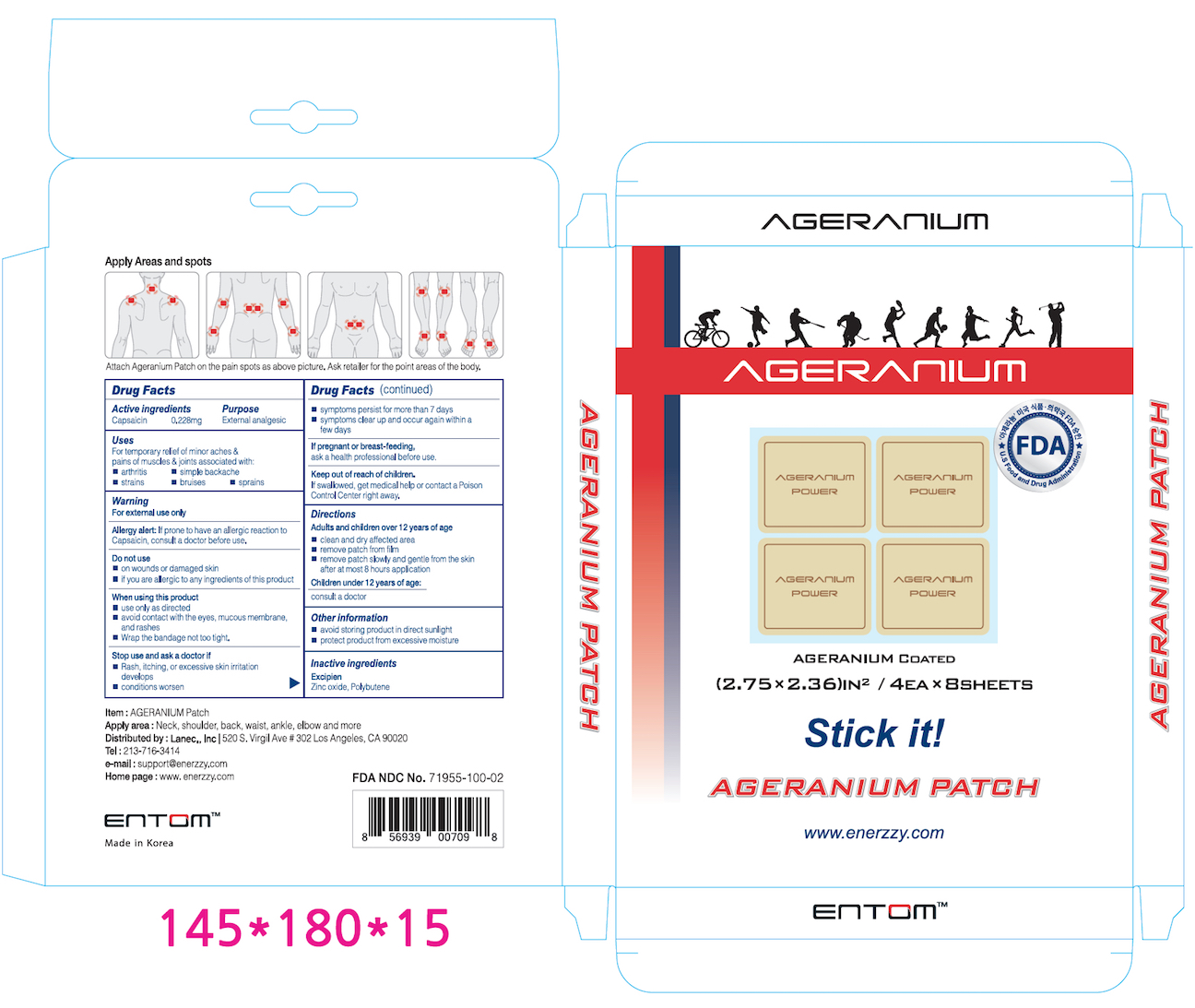 DRUG LABEL: Ageranium Patch
NDC: 71955-100 | Form: PATCH
Manufacturer: Entom Co., Ltd.
Category: otc | Type: HUMAN OTC DRUG LABEL
Date: 20171229

ACTIVE INGREDIENTS: CAPSAICIN 0.228 mg/99.13 mg
INACTIVE INGREDIENTS: POLYBUTENE (1400 MW); ZINC OXIDE

Ageranium Patch

Active ingredient

Capsacin 0.228mg

Purpose

External analgesic

Uses

For temporary relief of minor aches & pains of muscles & joints associated with:

- arthritis

- simple backace

- strains

- bruises

- sprains

Warnings

For external use only

Allergy alert: If prone to have an allergic reaction to Capsaicin, cunsult a doctor before use.

Do not use

- on wounds or damaged skin

- if you are allergic to any ingredients of this product

When using this product

- use only as directed

- avoid contact with the eyes, mucous membran, and rashes

- wrap the bandage not too tight

Stop use and ask a doctor if

- Rash, itching, or excessive skin irritation develops

- conditions worsen

- symptoms persist for more than 7 days

- symptoms clear up and occur again within a few days

If pregnant or breas-feeding

- ask a health professional before use.

Keep out of reach of children

Keep out or reach of children

- If swallowed, get medical help or contact a Poison Control Center right away.

Directions

Adults and children over 12 years of age

- clean and dry affected area

- remove patch from film

- remove patch slowly and gentle from the skin after at most 8 hours application

Children under 12 years of age:

consult a doctor

Inactive ingredients

Zinc oxide, Polybutene